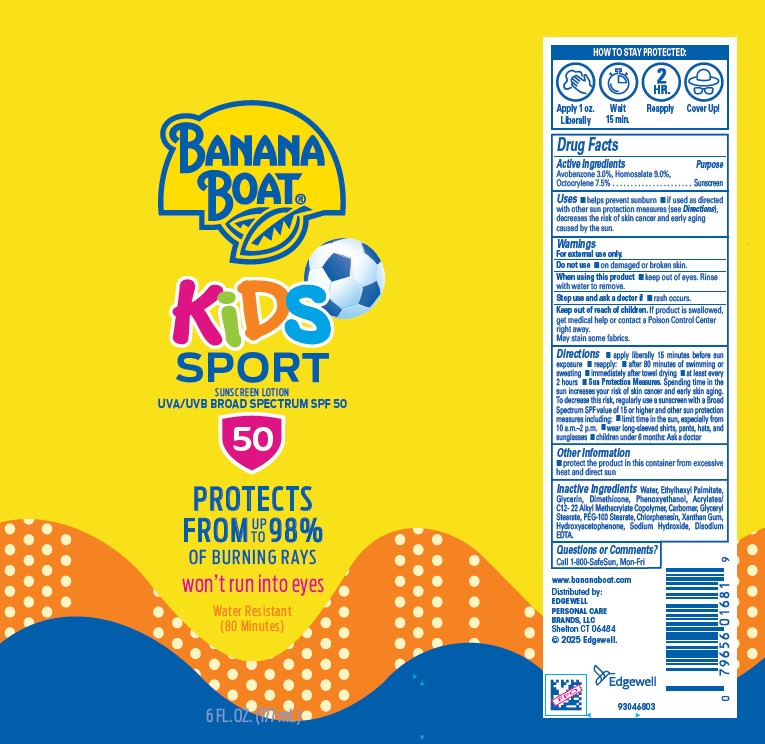 DRUG LABEL: Banana Boat
NDC: 63354-933 | Form: LOTION
Manufacturer: Edgewell Personal Care Brands LLC
Category: otc | Type: HUMAN OTC DRUG LABEL
Date: 20251015

ACTIVE INGREDIENTS: OCTOCRYLENE 7.5 g/100 g; HOMOSALATE 9 g/100 g; AVOBENZONE 3 g/100 g
INACTIVE INGREDIENTS: EDETATE DISODIUM; HYDROXYACETOPHENONE; PEG-100 STEARATE; CARBOMER; GLYCERYL STEARATE; XANTHAN GUM; DIMETHICONE; PHENOXYETHANOL; SODIUM HYDROXIDE; WATER; ETHYLHEXYL PALMITATE; GLYCERIN; CHLORPHENESIN

Active Ingredients

Avobenzone 3.0%, Homosalate 9.0%, Octocrylene 7.5%

Purpose

Sunscreen

Uses

• helps prevent sunburn • if used as directed with other sun protection measures (see Directions), decreases the risk of skin cancer and early aging caused by the sun.

Warnings

For external use only.
May stain some fabrics

Do not use

• on damaged or broken skin.

When using this product

• keep out of eyes. Rinse with water to remove.

Stop use and ask a doctor if

• rash occurs.

Keep out of reach of children.

If product is swallowed,get medical help or contact a Poison Control Center right away.

Directions

• apply liberally 15 minutes before sun exposure • reapply: • after 80 minutes of swimming or sweating • immediately after towel drying • at least every 2 hours • Sun Protection Measures. Spending time in the sun increases your risk of skin cancer and early skin aging.To decrease this risk, regularly use a sunscreen with a Broad Spectrum SPF value of 15 or higher and other sun protection measures including: • limit time in the sun, especially from 10 a.m.–2 p.m. • wear long-sleeved shirts, pants, hats, and sunglasses • children under 6 months: Ask a doctor

Other Information

• protect the product in this container from excessive heat and direct sun

Inactive Ingredients

Water, Ethylhexyl Palmitate,Glycerin, Dimethicone, Phenoxyethanol, Acrylates/ C12- 22 Alkyl Methacrylate Copolymer, Carbomer, Glyceryl Stearate, PEG-100 Stearate, Chlorphenesin, Xanthan Gum, Hydroxyacetophenone, Sodium Hydroxide, Disodium EDTA.

Questions or Comments?

Call 1-800-SafeSun, Mon-Fri

Prinicipal Display Panel

BANANA BOAT

KIDS

SPORT

SUNSCREEN LOTION

UVA/UVB BROAD SPECTRUM SPF 50

50

PROTECTS

FROM UP TO 98%

OF BURNING RAYS

won't run into eyes

Water Resistant

(80 Minutes)

6 FL OZ. (177 mL)